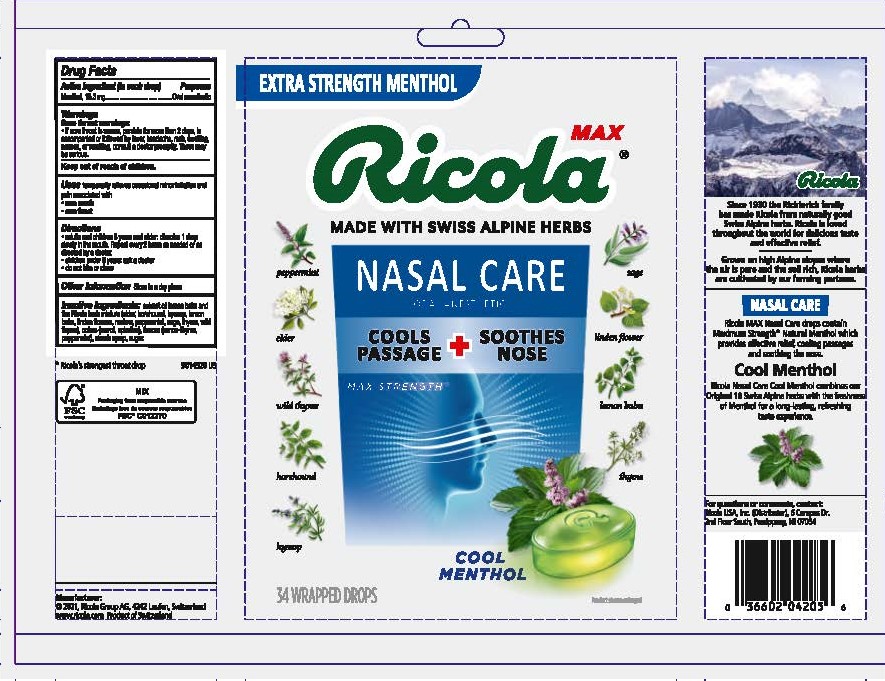 DRUG LABEL: RICOLA MAX NASAL CARE COOL MENTHOL
NDC: 63667-206 | Form: LOZENGE
Manufacturer: Ricola USA Inc.
Category: otc | Type: HUMAN OTC DRUG LABEL
Date: 20241210

ACTIVE INGREDIENTS: MENTHOL 15.3 mg/1 1
INACTIVE INGREDIENTS: SUCROSE

RICOLA MAX NASAL CARE COOL MENTHOL

Drug Facts

Purpose

Oral anesthetic

Active Ingredient (in each drop)

Menthol, 15.3 mg

Uses

temporarily relieves occasional minor irritation and pain associated with:

- sore mouth
- sore throat

Warnings

Sore throat warnings:

- if sore throat is severe, persists for more than 2 days, is accompanied or followed by fever, headache, rash, swelling, nausea, or vomiting, consult a doctor promptly. These may be serious.

Directions

- adults and children 6 years and older: dissolve 1 drop slowly in the mouth. Repeat every 2 hours as needed or as directed by a doctor.
- children under 6 years: ask a doctor
- do not bite or chew

Other Information

Store in a dry place

Inactive Ingredients

extract of lemon balm and the Ricola herb mixture (elder, horehound, hyssop, lemon balm, linden flowers, mallow, peppermint, sage, thyme, wild thyme), colors (carrot, spirulina), flavors (lemon-thyme, peppermint), starch syrup, sugar